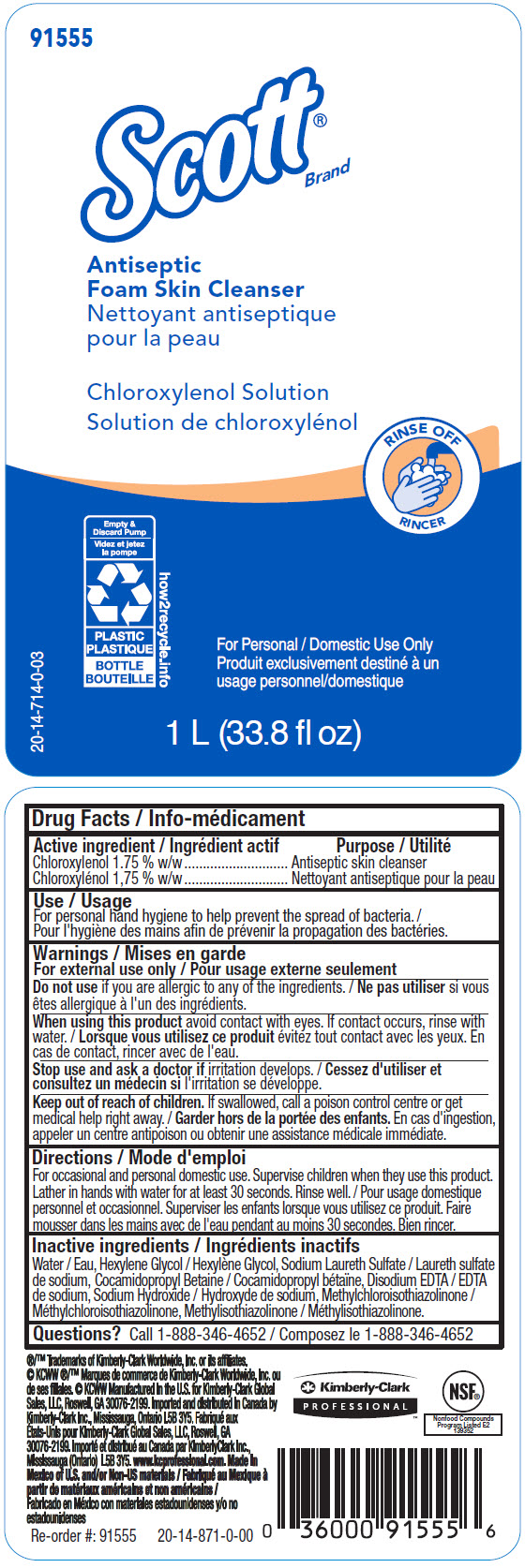 DRUG LABEL: SCOTT Antiseptic Foam Skin Cleanser
NDC: 55118-900 | Form: SOLUTION
Manufacturer: Kimberly-Clark
Category: otc | Type: HUMAN OTC DRUG LABEL
Date: 20241211

ACTIVE INGREDIENTS: Chloroxylenol 17.5 g/1 L
INACTIVE INGREDIENTS: HEXYLENE GLYCOL; SODIUM LAURETH-3 SULFATE; COCAMIDOPROPYL BETAINE; EDETATE DISODIUM ANHYDROUS; SODIUM HYDROXIDE; METHYLCHLOROISOTHIAZOLINONE; METHYLISOTHIAZOLINONE; Water

SCOTT® Antiseptic Foam Skin Cleanser

Drug Facts

Active ingredient

Chloroxylenol 1.75 % w/w

Purpose

Antiseptic skin cleanser

Use

For personal hand hygiene to help prevent the spread of bacteria.

Warnings

For external use only

Do not use if you are allergic to any of the ingredients.

When using this product avoid contact with eyes. If contact occurs, rinse with water.

Stop use and ask a doctor if irritation develops.

Keep out of reach of children. If swallowed, call a poison control centre or get medical help right away.

Directions

INDICATIONS AND USAGE

For occasional and personal domestic use. Supervise children when they use this product. Lather in hands with water for at least 30 seconds. Rinse well.

Inactive ingredients

Water, Hexylene Glycol, Sodium Laureth Sulfate, Cocamidopropyl Betaine, Disodium EDTA, Sodium Hydroxide, Methylchloroisothiazolinone, Methylisothiazolinone

Questions?

Call 1-888-346-4652

Imported and distributed in Canada by
Kimberly-Clark Inc., Mississauga, Ontario L5B 3Y5

PRINCIPAL DISPLAY PANEL - 1 L Bottle Label

91555

Scott®
Brand

Antiseptic
Foam Skin Cleanser

Chloroxylenol Solution

RINSE OFF

Empty &
Discard Pump
PLASTIC
BOTTLE
how2recycle.info

For Personal / Domestic Use Only

20-14-714-0-03

1 L (33.8 fl oz)